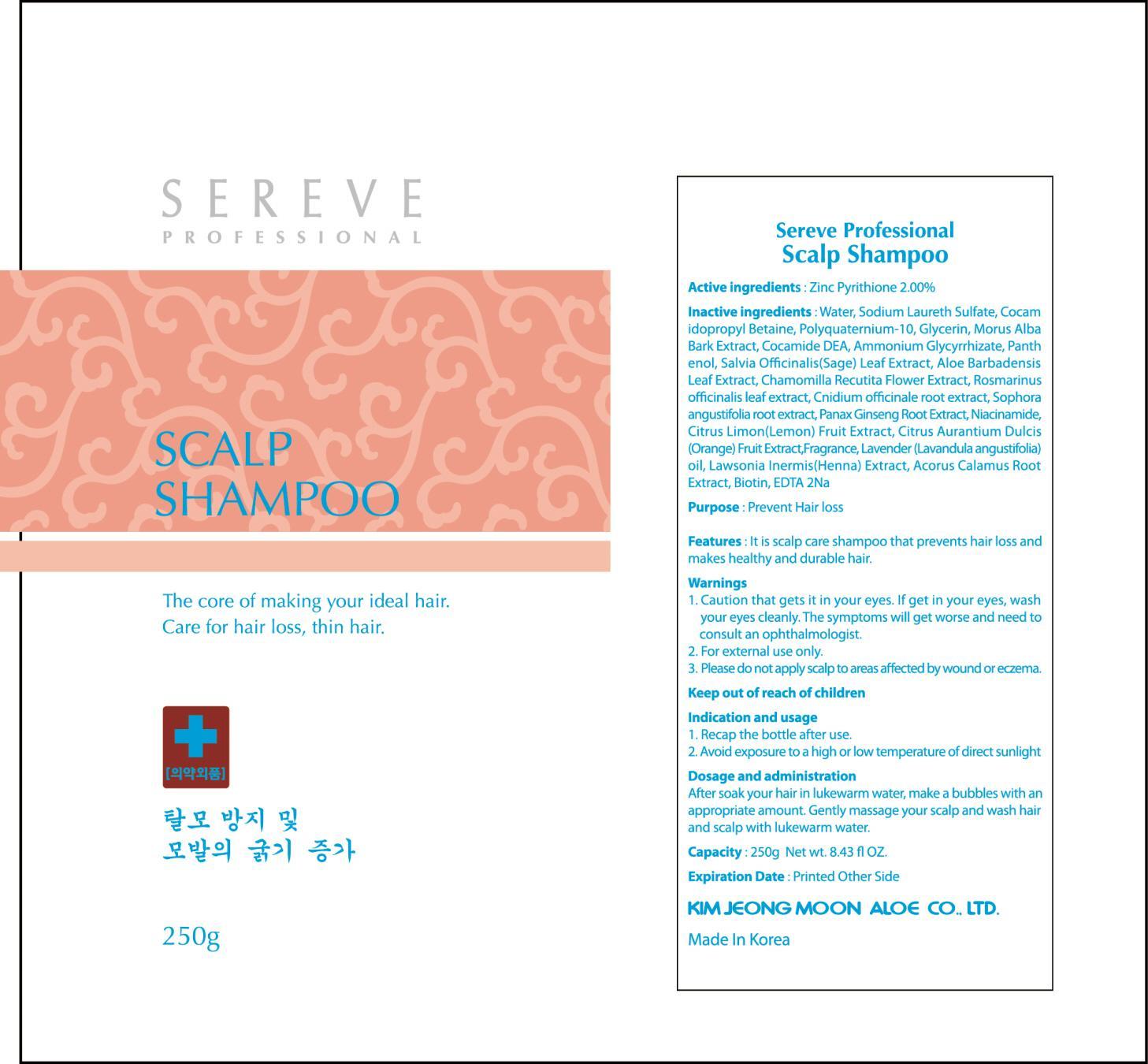 DRUG LABEL: Sereve Professional Scalp
NDC: 50410-080 | Form: SHAMPOO
Manufacturer: Kimjeongmoon Aloe Co., Ltd.
Category: otc | Type: HUMAN OTC DRUG LABEL
Date: 20150225

ACTIVE INGREDIENTS: PYRITHIONE ZINC 5 g/250 g
INACTIVE INGREDIENTS: Water; Sodium Laureth Sulfate

ACTIVE INGREDIENT

Active ingredients: Zinc Pyrithione 2.00%

INACTIVE INGREDIENT

Inactive ingredients: Water, Sodium Laureth Sulfate, Cocamidopropyl Betaine, Polyquaternium-10, Glycerin, Morus Alba Bark Extract, Cocamide DEA, Ammonium Glycyrrhizate, Panthenol, Salvia Officinalis (Sage) Leaf Extract, Aloe Barbadensis Leaf Extract, Chamomilla Recutita Flower Extract, Rosmarinus officinalis leaf extract, Cnidium officinale root extract, Sophora angustifolia root extract, Panax Ginseng Root Extract, Niacinamide, Citrus Limon (Lemon) Fruit Extract, Citrus Aurantium Dulcis (Orange) Fruit Extract, Fragrance, Lavender (Lavandula angustifolia) oil, Lawsonia Inermis (Henna) Extract, Acorus Calamus Root Extract, Biotin, EDTA 2Na

PURPOSE

Purpose: Prevent Hair loss

WARNINGS

Warnings: 1. Caution that gets it in your eyes. If get in your eyes, wash your eyes cleanly. The symptoms will get worse and need to consult an ophthalmologist. 2. For external use only. 3. Please do not apply scalp to areas affected by wound or eczema.

KEEP OUT OF REACH OF CHILDREN

INDICATIONS & USAGE

Indication and usage: 1. Recap the bottle after use. 2. Avoid exposure to a high or low temperature of direct sunlight

DOSAGE & ADMINISTRATION

Dosage and administration: After soak your hair in lukewarm water, make a bubbles with an appropriate amount. Gently massage your scalp and wash hair and scalp with lukewarm water.

PACKAGE LABEL.PRINCIPAL DISPLAY PANEL

Image of carton